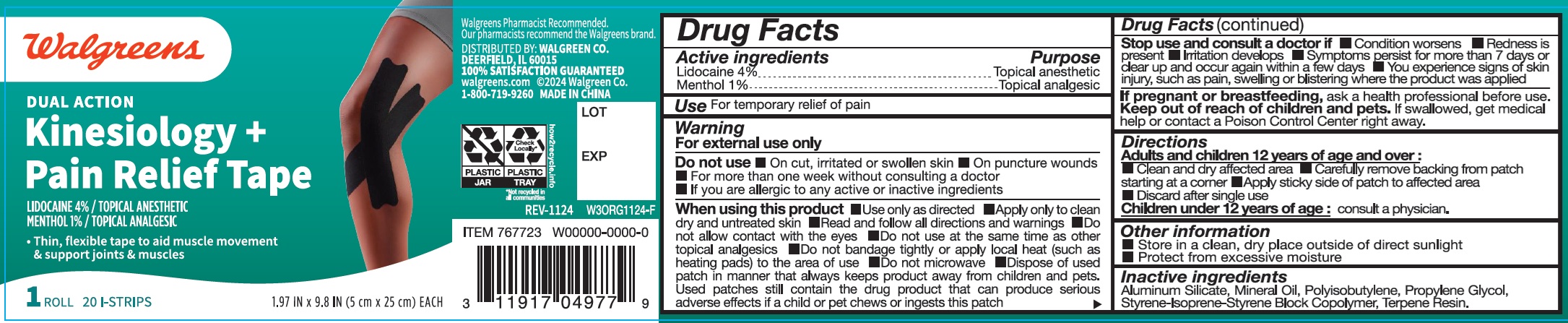 DRUG LABEL: Walgreens Kinesiology Pain Relief
NDC: 0363-9657 | Form: TAPE
Manufacturer: Walgreen Co.
Category: otc | Type: HUMAN OTC DRUG LABEL
Date: 20241219

ACTIVE INGREDIENTS: LIDOCAINE 4 mg/100 mg; MENTHOL 1 mg/100 mg
INACTIVE INGREDIENTS: ALUMINUM SILICATE; MINERAL OIL; PROPYLENE GLYCOL; STYRENE/ISOPRENE/STYRENE BLOCK COPOLYMER; TERPENE RESIN

Walgreens Kinesiology + Pain Relief Tape

Active ingredients

Lidocaine 4%

Menthol 1%

Purpose

Topical anesthetic

Topical analgesic

Use

For temporary relief of pain

Warning

For external use only

Do not use

- On cut, irritated or swollen skin
- On puncture wounds
- For more than one week without consulting a doctor
- If you are allergic to any active or inactive ingredients

When using this product

- Use only as directed
- Apply only to clean dry and untreated skin
- Read and follow all directions and warnings
- Do not allow contact with the eyes
- Do not use at the same time as other topical analgesics
- Do not bandage tightly or apply local heat (such as heating pads) to the area of use
- Do not microwave
- Dispose of used patch in manner that always keeps product away from children and pets. Used patches still contain the drug product that can produce serious adverse effects if a child or pet chews or ingests this patch

Stop use and consult a doctor if

- Condition worsens
- Redness is present
- Irritation develops
- Symptoms persist for more than 7 days or clear up and occur again within a few days
- You experience signs of skin injury, such as pain, swelling or blistering where the product was applied

If pregnant or breastfeeding,

ask a health professional before use.

Keep out of reach of children and pets.

If swallowed, get medical help or contact a Poison Control Center right away.

Directions

Adults and children 12 years of age and over:

- Clean and dry affected area.
- Carefully remove backing from patch starting at a corner
- Apply sticky side of patch to affected area
- Discard after single use

Children under 12 years of age: consult a physician.

Other information

- Store in a clean, dry place outside of direct sunlight
- Protect from excessive moisture

Inactive ingredients

Aluminum Silicate, Mineral Oil, Polyisobutylene, Propylene Glycol, Styrene-Isoprene-Styrene Block Copolymer, Terpene Resin.